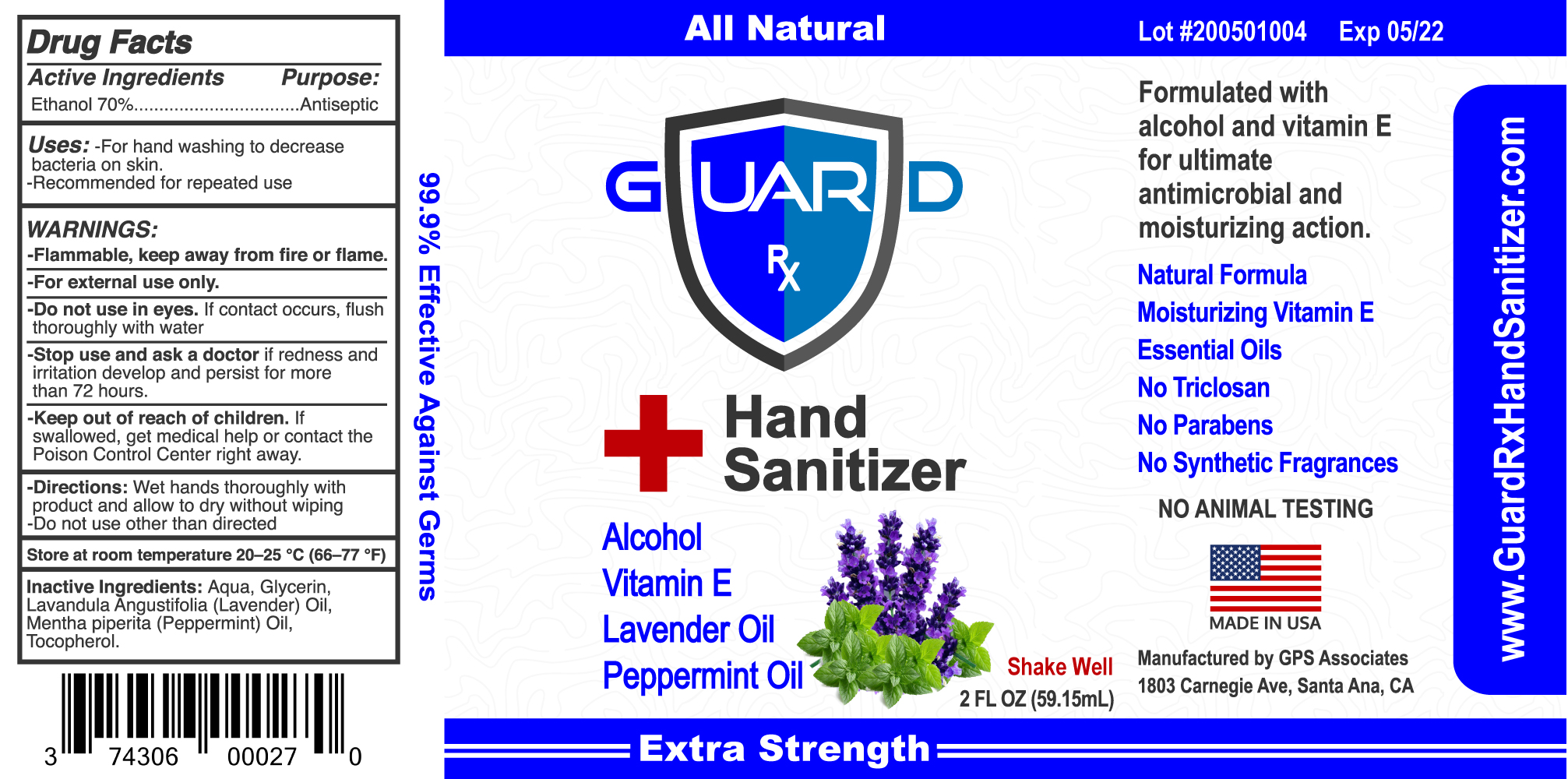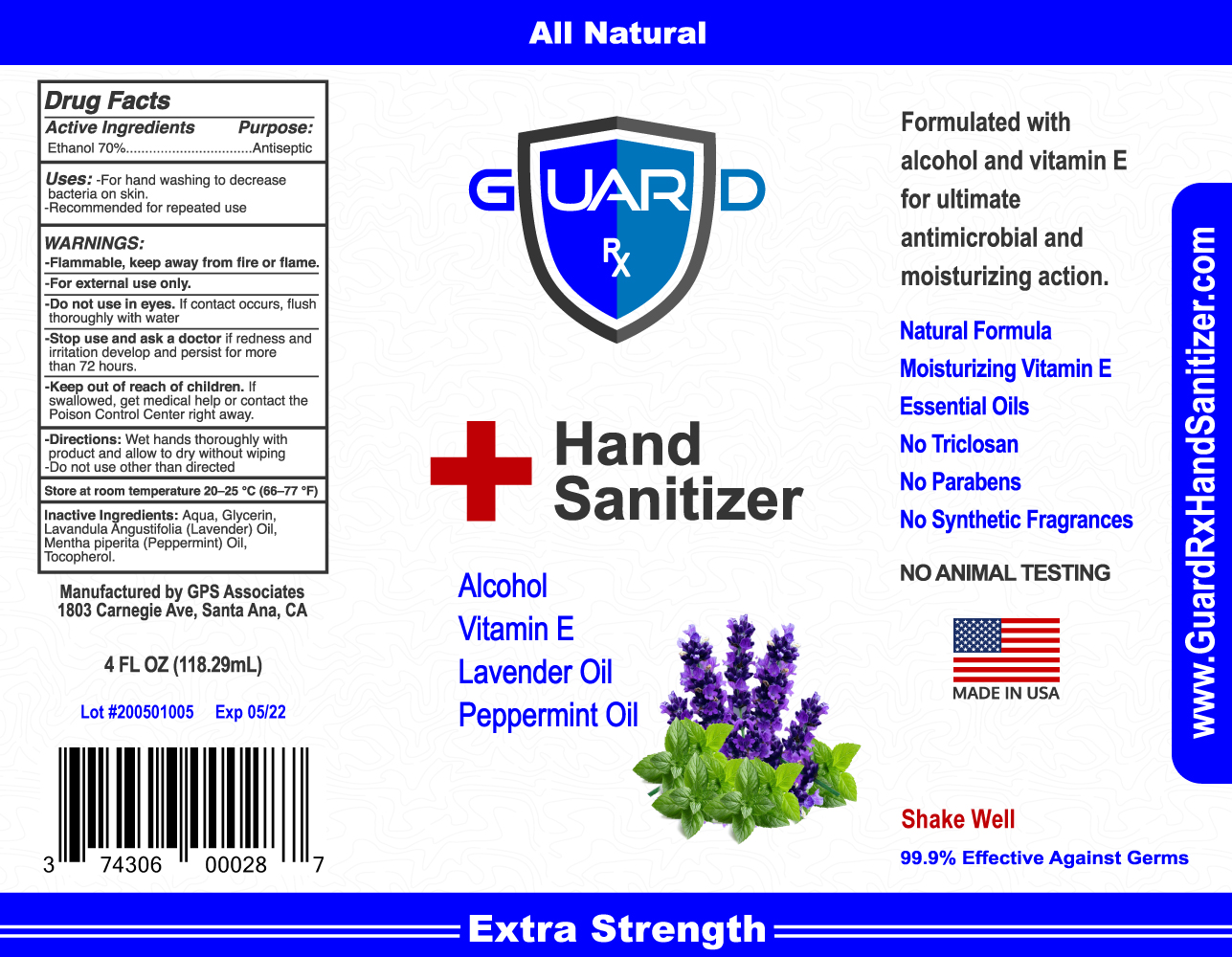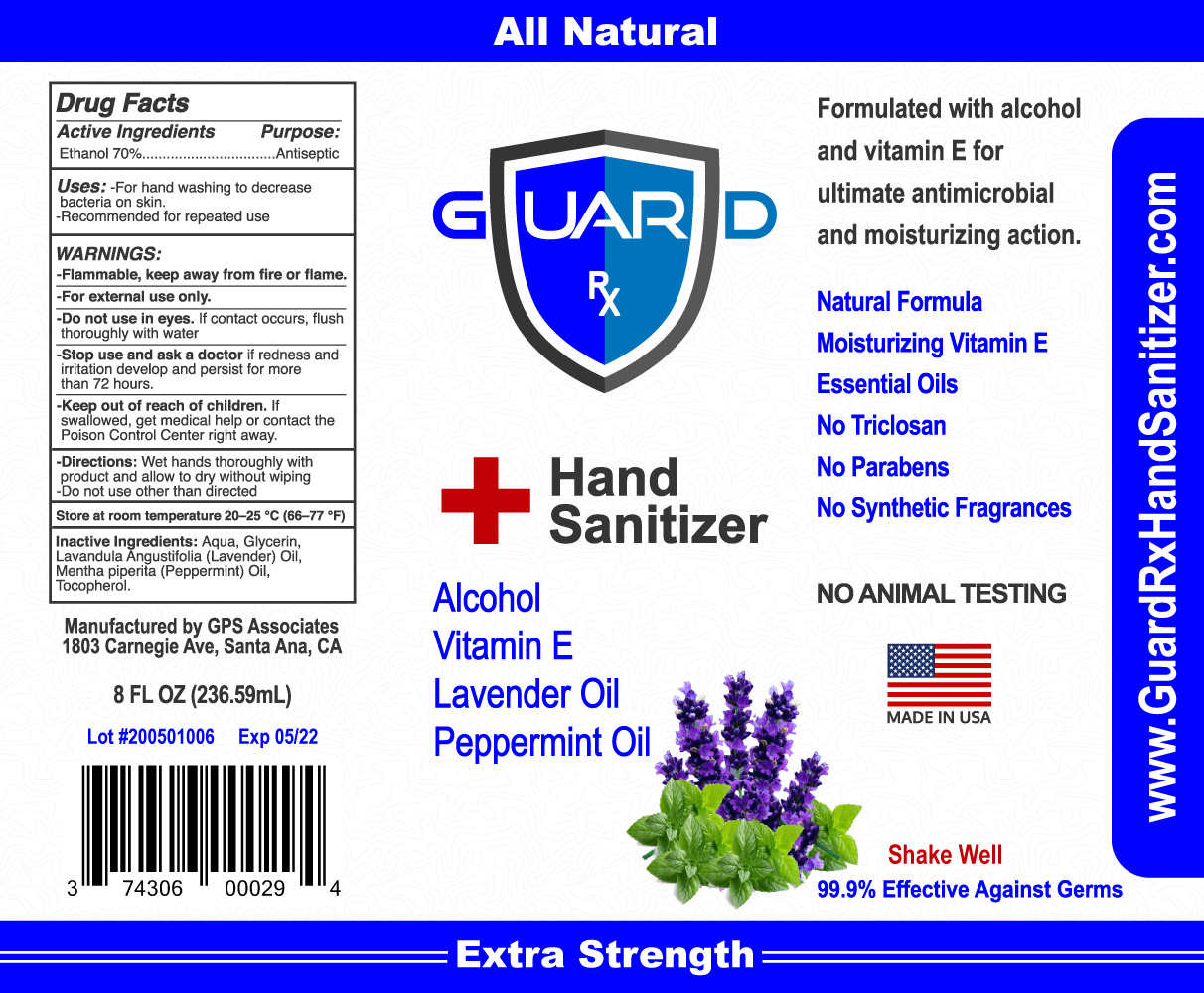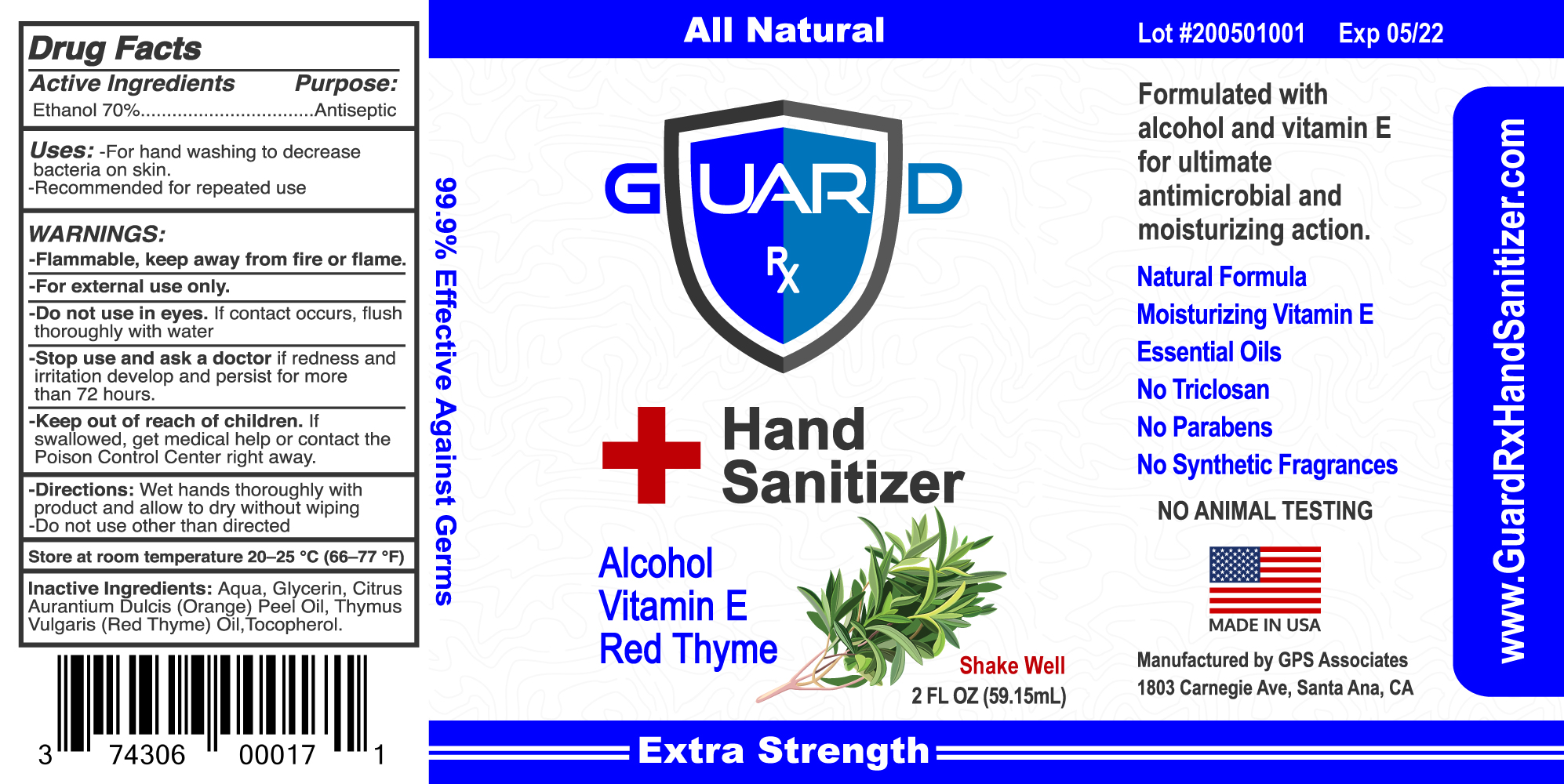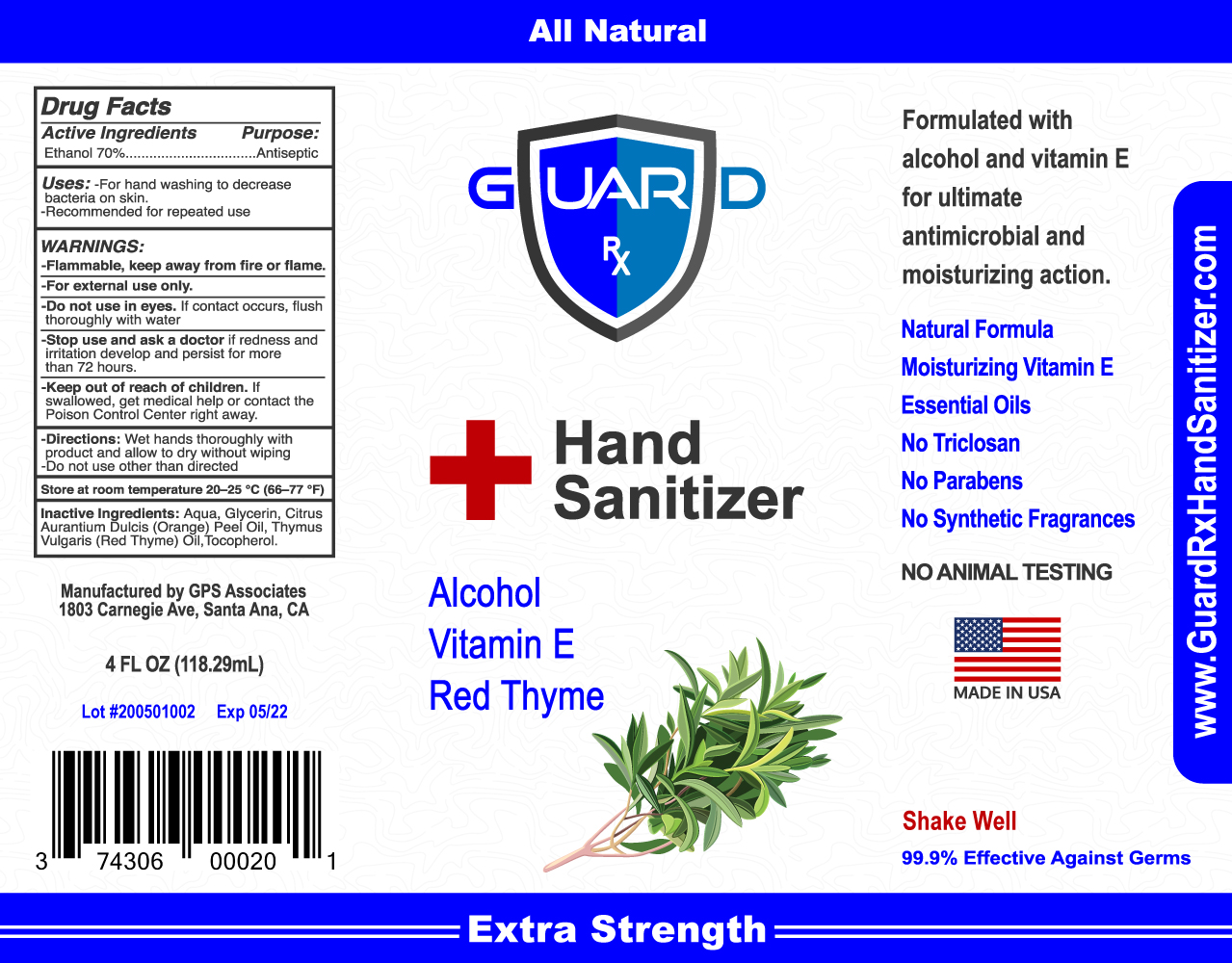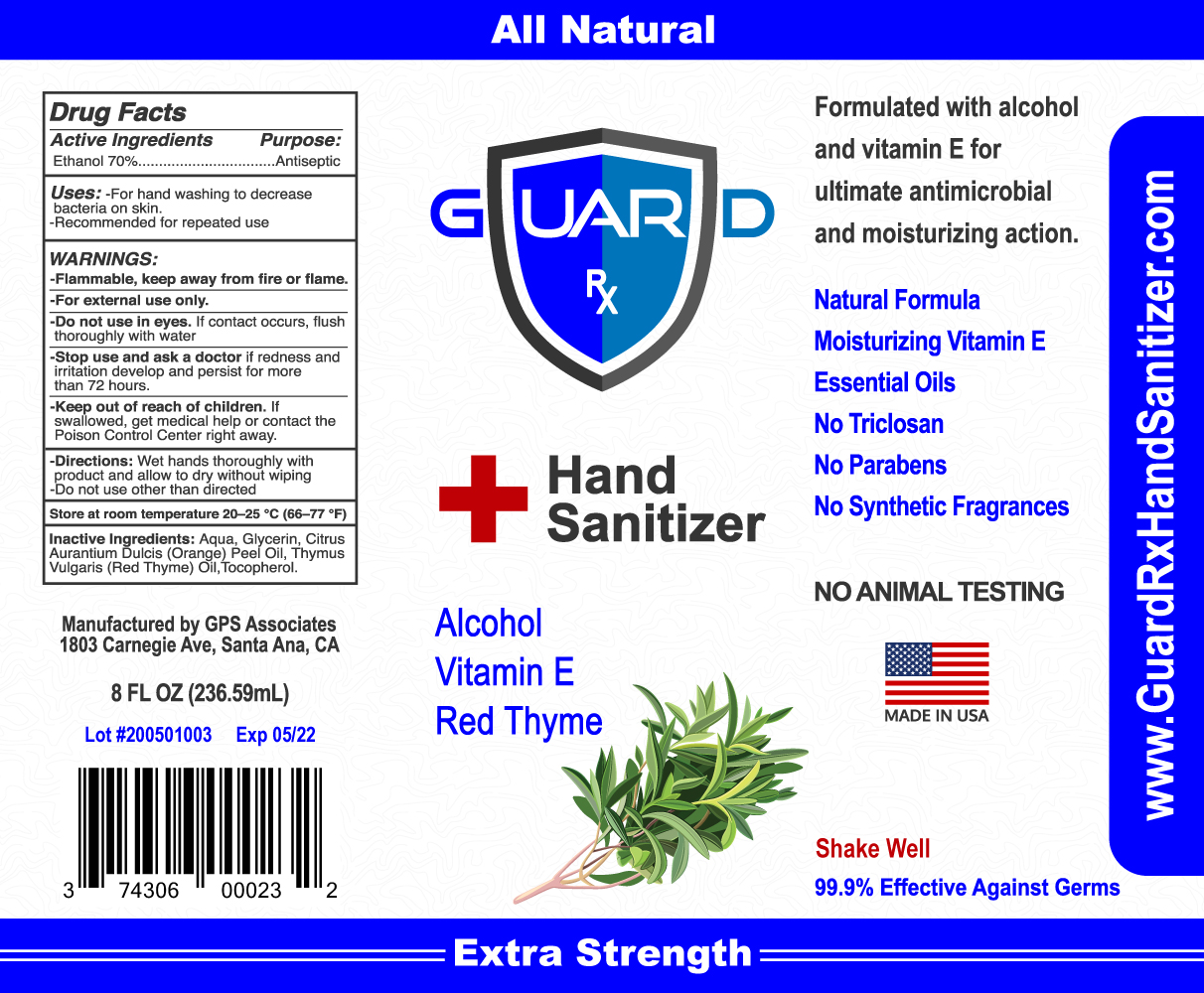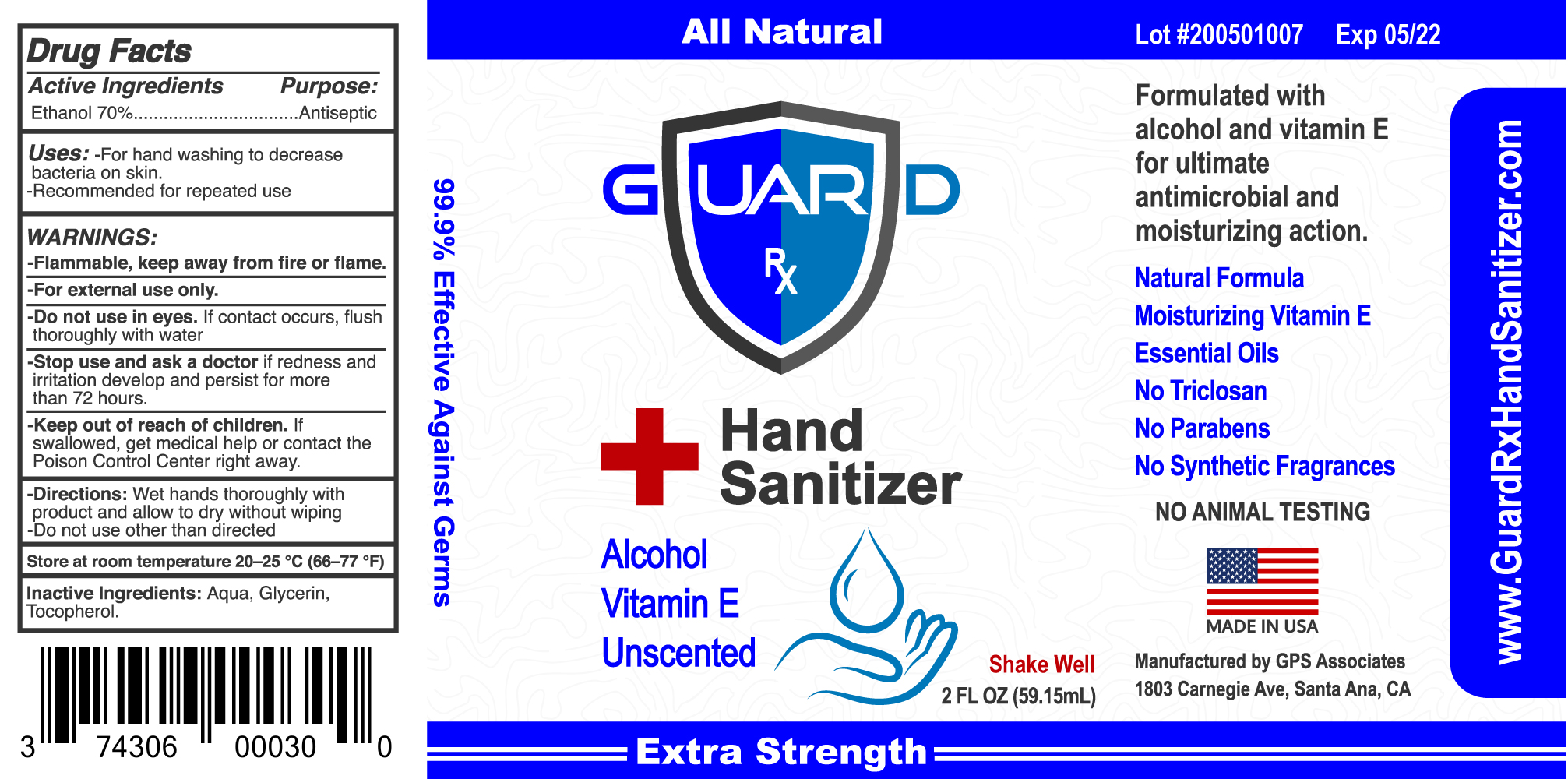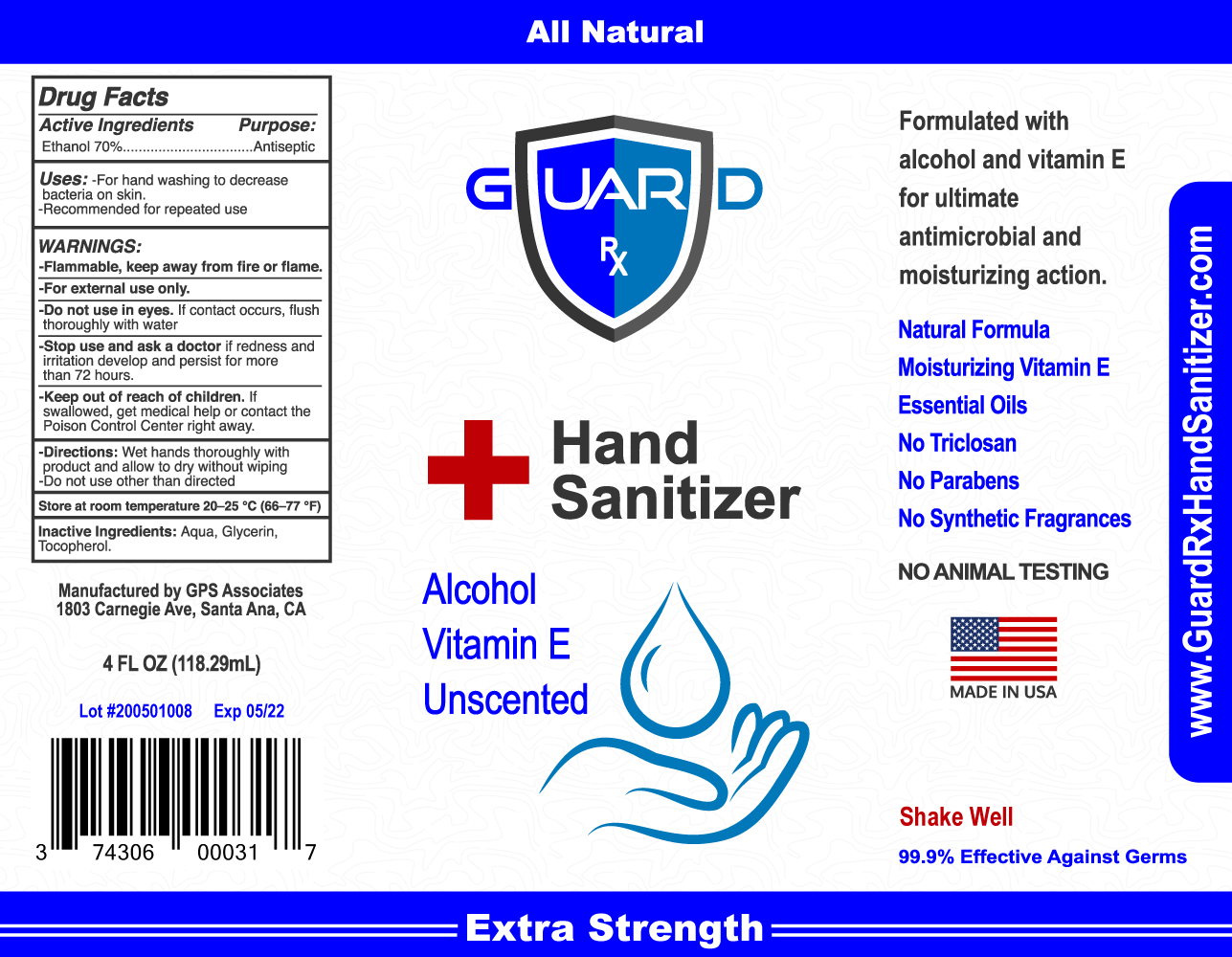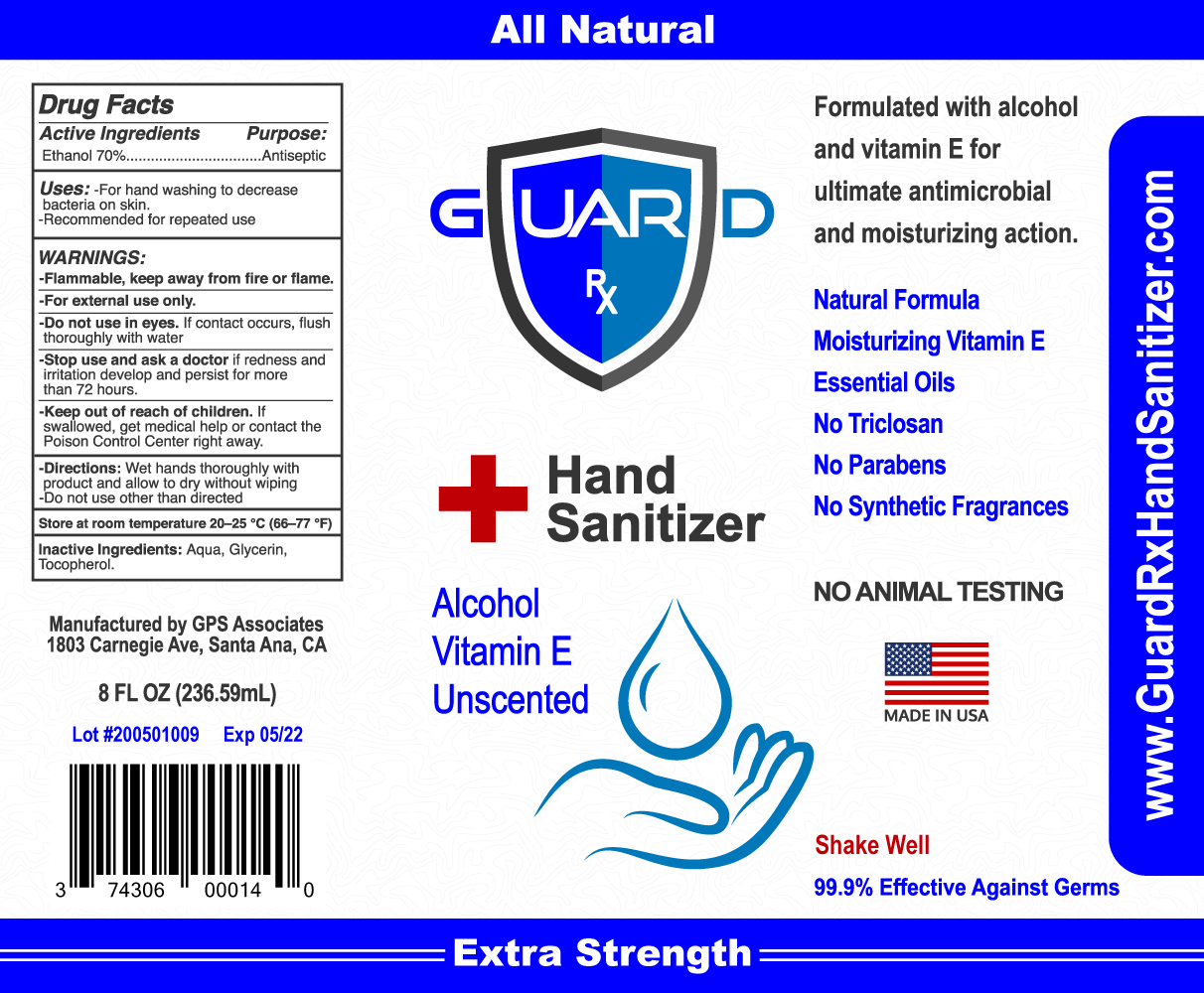 DRUG LABEL: GuardRx Unscented Extra Strength
NDC: 74306-135 | Form: LIQUID
Manufacturer: GPS Associates
Category: otc | Type: HUMAN OTC DRUG LABEL
Date: 20200504

ACTIVE INGREDIENTS: ALCOHOL 70 mL/100 mL
INACTIVE INGREDIENTS: WATER; .ALPHA.-TOCOPHEROL, DL-; GLYCERIN

ACTIVE INGREDIENT

Ethanol 70%

Purpose:

Antiseptic

Uses:

-For hand washing to decrease bacteria on skin.

-Recommended for repeated use.

WARNINGS:

-Flammable, keep away from children.

WHEN USING

-For external use only.

-Do not use in eyes. If contact occurs, flush thoroughly with water.

-Stop use and ask doctor if redness and irritation develop and persist for more than 72 hours.

-Keep out of reach of children. If swallowed, get medical help or contact the Poison Control Center right away.

Directions:

Wet hands thoroughly with product and allow to dry without wiping.

-Do not use other than directed.

STORAGE AND HANDLING

Store at room temperature 20-25 °C (66-77 °F)

Inactive Ingredients:

Aqua, Glycerin, Citrus Aurantium Dulcis (Orange) Peel Oil, Thymus Vulgaris (Red Thyme) Oil, Tocopherol.

ACTIVE INGREDIENT

Ethanol 70%

Purpose:

Antiseptic

Uses:

-For hand washing to decrease bacteria on skin.

-Recommended for repeated use.

WARNINGS:

-Flammable, keep away from children.

WHEN USING

-For external use only.

-Do not use in eyes. If contact occurs, flush thoroughly with water.

-Stop use and ask doctor if redness and irritation develop and persist for more than 72 hours.

-Keep out of reach of children. If swallowed, get medical help or contact the Poison Control Center right away.

Directions:

Wet hands thoroughly with product and allow to dry without wiping.

-Do not use other than directed.

STORAGE AND HANDLING

Store at room temperature 20-25 °C (66-77 °F)

Inactive Ingredients:

Aqua, Glycerin, Lavandula Angustifolia (Lavender) Oil, Mentha Piperita (Peppermint) Oil, Tocopherol.

ACTIVE INGREDIENT

Ethanol 70%

Purpose:

Antiseptic

Uses:

-For hand washing to decrease bacteria on skin.

-Recommended for repeated use.

WARNINGS:

-Flammable, keep away from children.

WHEN USING

-For external use only.

-Do not use in eyes. If contact occurs, flush thoroughly with water.

-Stop use and ask doctor if redness and irritation develop and persist for more than 72 hours.

-Keep out of reach of children. If swallowed, get medical help or contact the Poison Control Center right away

Directions:

Wet hands thoroughly with product and allow to dry without wiping.

-Do not use other than directed.

STORAGE AND HANDLING

Store at room temperature 20-25 °C (66-77 °F)

Inactive Ingredients:

Aqua, Glycerin, Tocopherol.